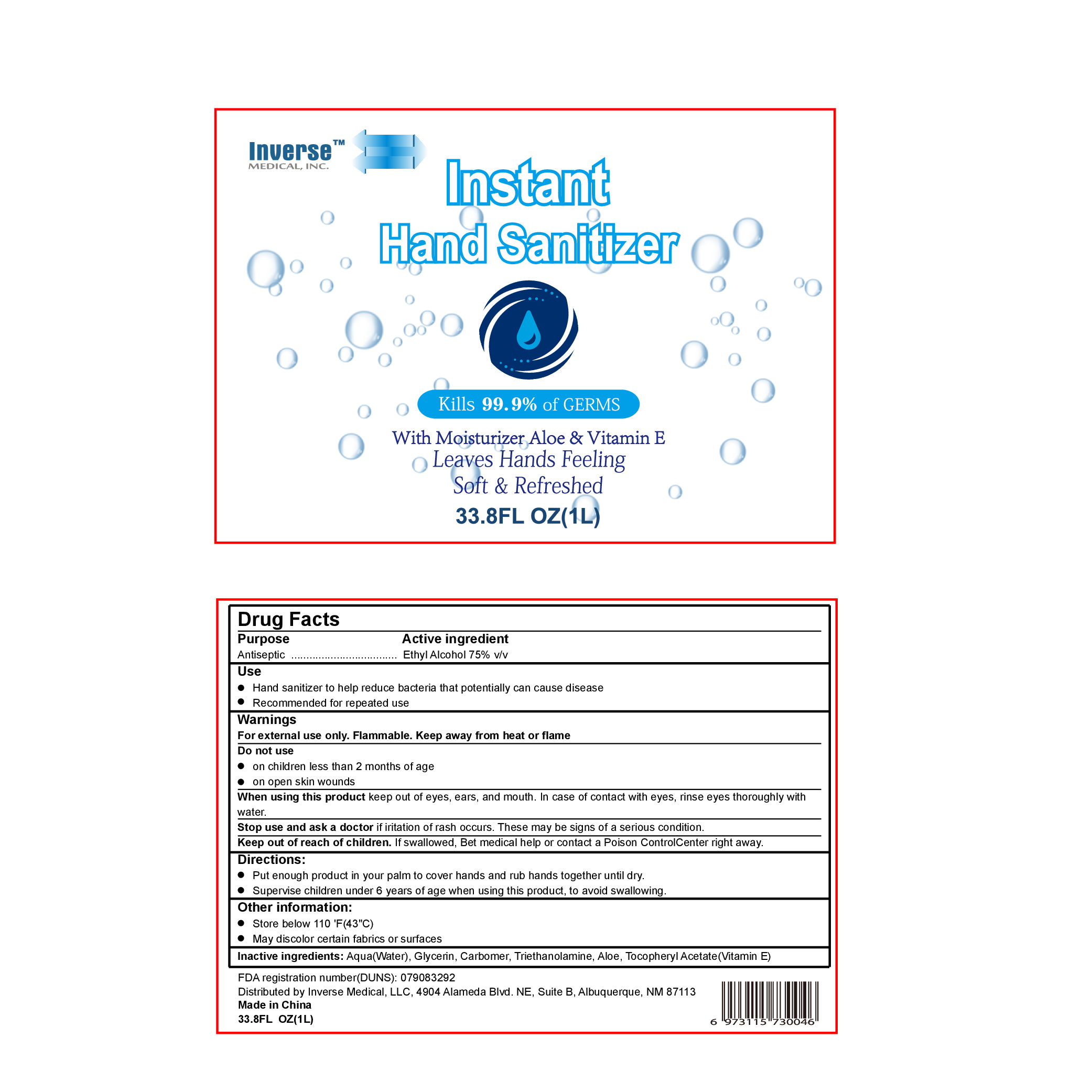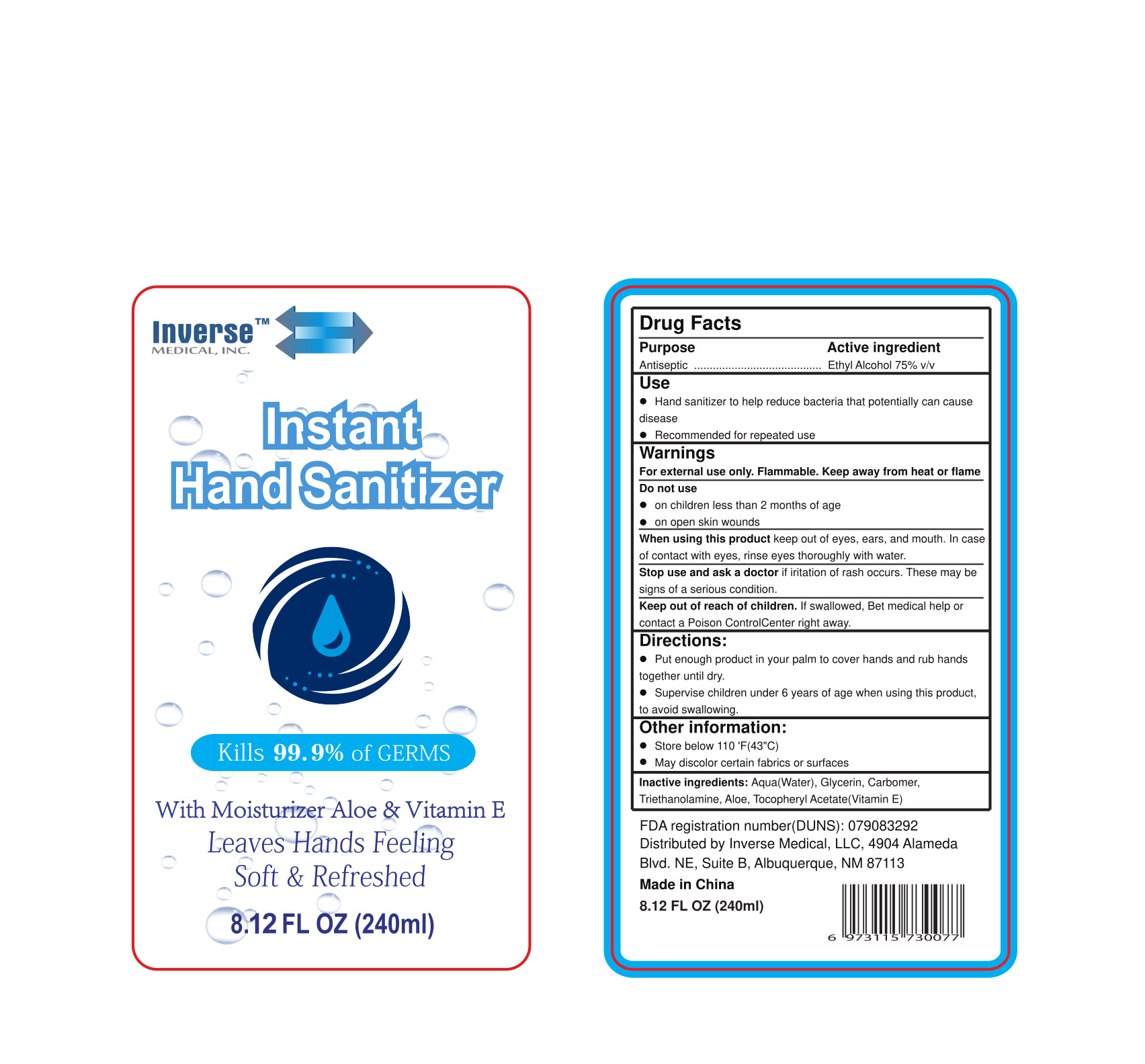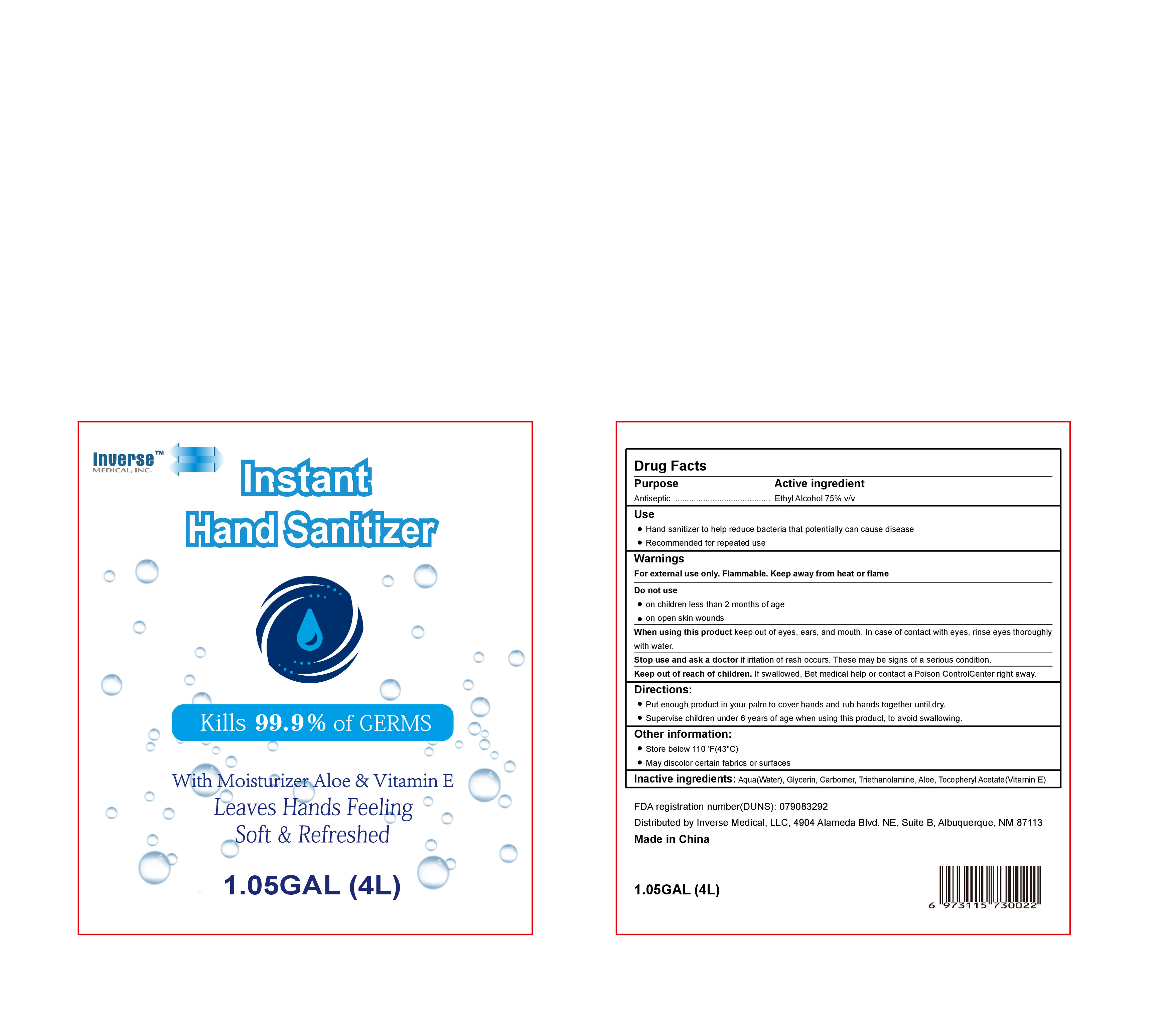 DRUG LABEL: Inverse Medical Instant Hand Sanitizer
NDC: 80507-001 | Form: GEL
Manufacturer: Inverse Medical LLC
Category: otc | Type: HUMAN OTC DRUG LABEL
Date: 20200921

ACTIVE INGREDIENTS: ALCOHOL 75 mL/100 mL
INACTIVE INGREDIENTS: GLYCERIN; WATER; ALPHA-TOCOPHEROL ACETATE; ALOE; CARBOMER HOMOPOLYMER, UNSPECIFIED TYPE; TROLAMINE

Inverse Medical - Instant Hand Sanitizer

Active Ingredient(s)

Ethyl Alcohol 75% v/v

Purpose

Antiseptic

Use

Hand Sanitizer to help reduce bacteria that potentially can cause disease

Recommended for repeated use

Warnings

For external use only. Flammable. Keep away from heat or flame

Do not use

- on children less than 2 months of age
- on open skin wounds

When using this product keep out of eyes, ears, and mouth. In case of contact with eyes, rinse eyes thoroughly with water.

Stop use and ask a doctor if irritation of rash occurs. These may be signs of a serious condition.

Keep out of reach of children. If swallowed, Bet medical help or contact a Poison ControlCenter right away.

Directions

- Place enough product in your palm to cover hands and rub hands together until dry.
- Supervise children under 6 years of age when using this product, to avoid swallowing.

Other information

- Store below 110 'F(43"C)
- May discolor certain fabrics or surfaces

Inactive ingredients

Aqua(water), Glycerin, Carbomer, Trierthanolamine, Aloe, Tocopheryl Acetate (Vitamin E)